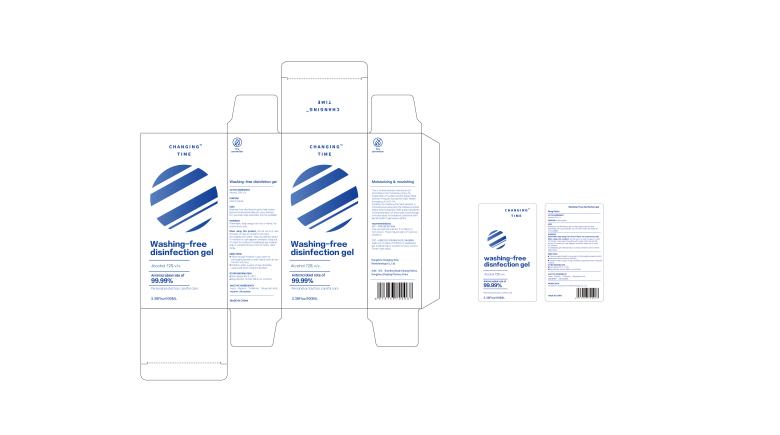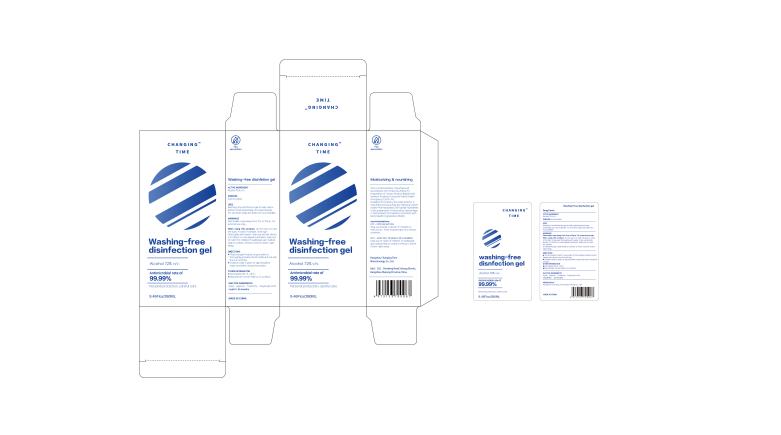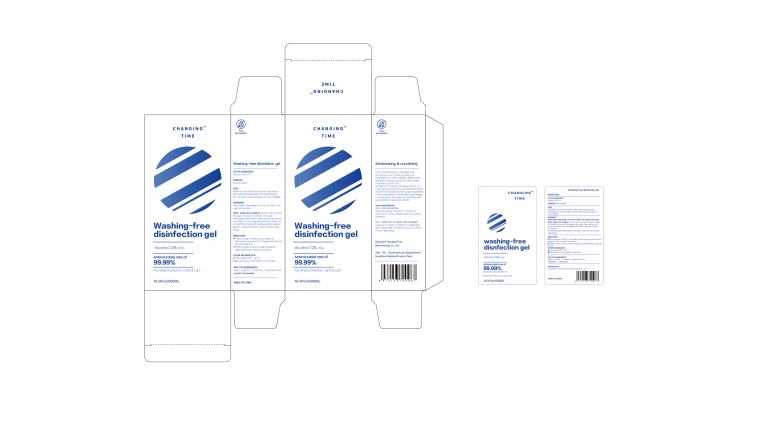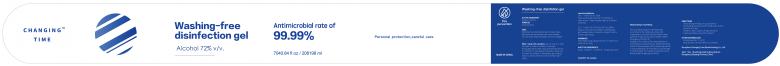 DRUG LABEL: Washing-free disinfection gel
NDC: 75153-001 | Form: GEL
Manufacturer: Hangzhou Changing Time Biotechnology Co., Ltd.
Category: otc | Type: HUMAN OTC DRUG LABEL
Date: 20200423

ACTIVE INGREDIENTS: ALCOHOL 72 mL/100 mL
INACTIVE INGREDIENTS: GLYCERIN; POLYACRYLIC ACID (250000 MW); WATER; TROLAMINE

Washing-free disinfection gel

ACTIVE INGREDIENT

Alcohol 72%v/v.

PURPOSE

Antimicrobial

USES

Washing-free disinfection gel to help reduce bacteria that potentially can cause disease.

For use when soap and water are not available.

WARNINGS

Flammable.Keep away from fire or flame.For external use only.

When using this product

do not use in or near the eyes.In case of contact,rinse eyes thoroughly with water.Stop use and ask doctor if irritation or rash appears and lasts.Keep out of reach for children.If swallowed,get medical help or contact a Poison Control Center right away.

Stop use and ask a doctor if irritation or rash occurs.These may be signs of a serious condition.

Keep out of reach of children.If swallowed,get medical help or contact a Poison Control Center right away.

DIRECTIONS

Place enough Product in your palm to thoroughly spread on both hands and rub into the skin until dry.

Children under 6 years of age should be supervised when using this product.

OTHER INFORMATION

Store below 106°F.(4I℃)

May discolor certain fabrics or surfaces.

INACTIVE INGREDIENTS

Aqua,Glycerin,Trolamine, Polyacrylic Acid.